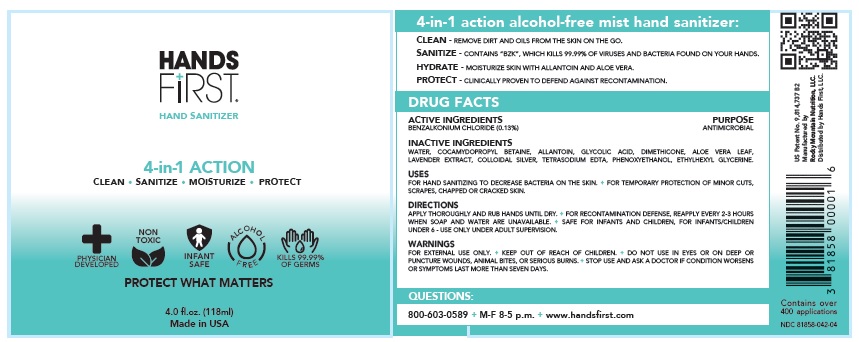 DRUG LABEL: HANDS FIRST TM
NDC: 81858-042 | Form: SPRAY
Manufacturer: Hands First, LLC.
Category: otc | Type: HUMAN OTC DRUG LABEL
Date: 20211028

ACTIVE INGREDIENTS: BENZALKONIUM CHLORIDE 1.3 mg/1 mL
INACTIVE INGREDIENTS: WATER; COCAMIDOPROPYL BETAINE; ALLANTOIN; GLYCOLIC ACID; DIMETHICONE; ALOE VERA LEAF; SILVER; ENGLISH LAVENDER OIL; EDETATE SODIUM; PHENOXYETHANOL; ETHYLHEXYLGLYCERIN

Drug Facts

Active Ingredient

Benzalkonium Chloride 0.13%

Purpose

Antimicrobial

Use

- For handwashing to decrease bacteria on the skin
- For temporary protection of minor cuts, scrapes, burns and chapped or cracked skin

Warnings

- For external use only.
- Keep out of the reach of children. If swallowed, get medical help, or contact a Poison Control Center right away.
- Do not use in the eyes.
- Do not use on deep or puncture wounds, animal bites or serious burns.
- Extended use may increase risk of sunburn.

Stop use and ask a doctor if:

- symptoms worsen, last for more than seven days, or new symptoms occur at any time

Direction

- Uses as needed.
- Remove cap and pump foam into palm of hands.
- Rub foam onto hands.
- Allow to air dry.

Other information

- save carton for full directions and warnings
- store between 20 to 25oC (68 to 77oF)

Inactive ingredients

water, cocamidopropyl betaine , allantoin, glycolic acid, dimethicone, aloe vera leaf, lavender extract, colloidal silver, tetrasodium EDTA, phenoxyethanol, ethylhexyl glycerine.

Questions?

Call 1-800-603-0589 between 9am and 5pm (EST) Monday through Friday or visit www.handsfirst.com

PACKAGE LABEL.PRINCIPAL DISPLAY PANEL

Hands First

4 in 1 action

Alcohol Free Spray

Hand Sanitizer

Doctor created and hospital tested

Sanitize anytime, anywhere

Temporarily protect minor cuts and scrapes

Hydrate your skin

Clean without water

Kills 99.99% of germs

4 fl oz (118mL)